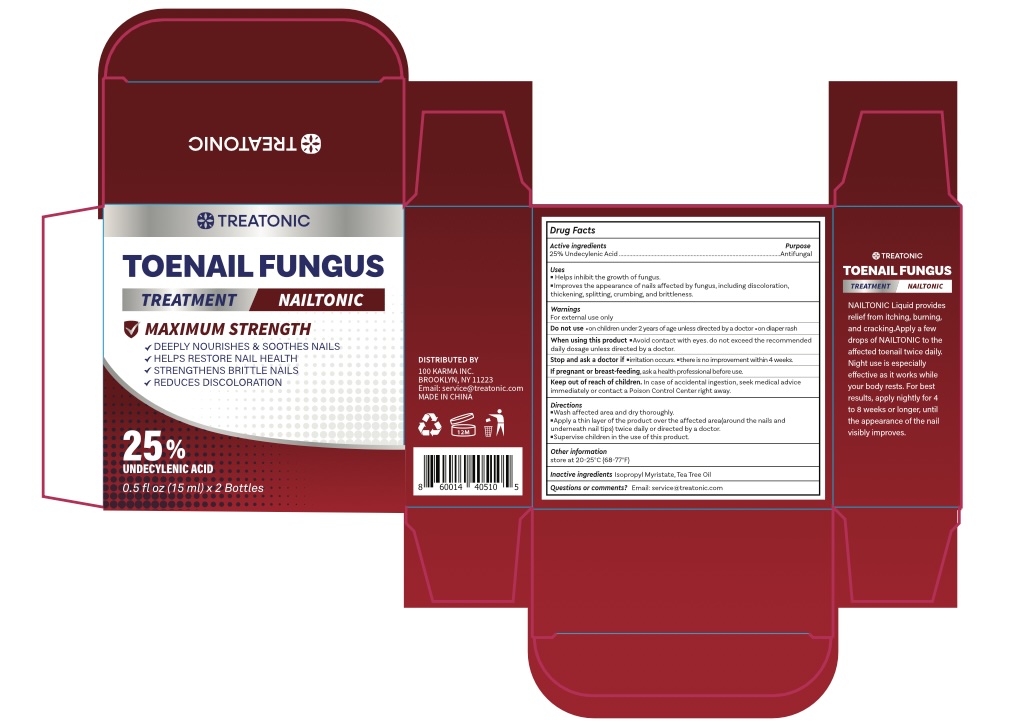 DRUG LABEL: TOENAIL FUNGUS TREATMENT
NDC: 85569-005 | Form: LIQUID
Manufacturer: 100 KARMA INC
Category: otc | Type: HUMAN OTC DRUG LABEL
Date: 20260301

ACTIVE INGREDIENTS: UNDECYLENIC ACID 25 g/100 mL
INACTIVE INGREDIENTS: TEA TREE OIL; ISOPROPYL MYRISTATE

Update-85569-005-01

ACTIVE INGREDIENT

25% Undecylenic Acid

PURPOSE

Antifungal

INDICATIONS AND USAGE

- Helps inhibit the growth of fungus.
- Improves the appearance of nails affected by fungus, including discoloration, thickening, splitting, crumbing, and brittleness.

WARNINGS

For external use only

Do not use

- on children under 2 years of age unless directed by a doctor
- on diaper rash

WHEN USING

avoid contact with eyes. Do not exceed the recommended daily dosage unless directed by a doctor.

STOP USE

Stop and ask a doctor if ▪ irritation occurs. ▪ there is no improvement within 4 weeks.

PREGNANCY OR BREAST FEEDING

If pregnant or breast-feeding, ask a health professional before use.

Keep out of reach of children. In case of accidental ingestion, seek medical advice immediately or contact a Poison Control Center right away.

DOSAGE AND ADMINISTRATION

▪ Wash affected area and dry thoroughly.
▪ Apply a thin layer of the product over the affected area (around the nails and underneath nail tips) twice daily or directed by a doctor.
▪ Supervise children in the use of this product.

OTHER SAFETY INFORMATION

store at 20-25°C (68-77°F)

INACTIVE INGREDIENT

Isopropyl Myristate, Tea Tree Oil

QUESTIONS

Email: service@treatonic.com